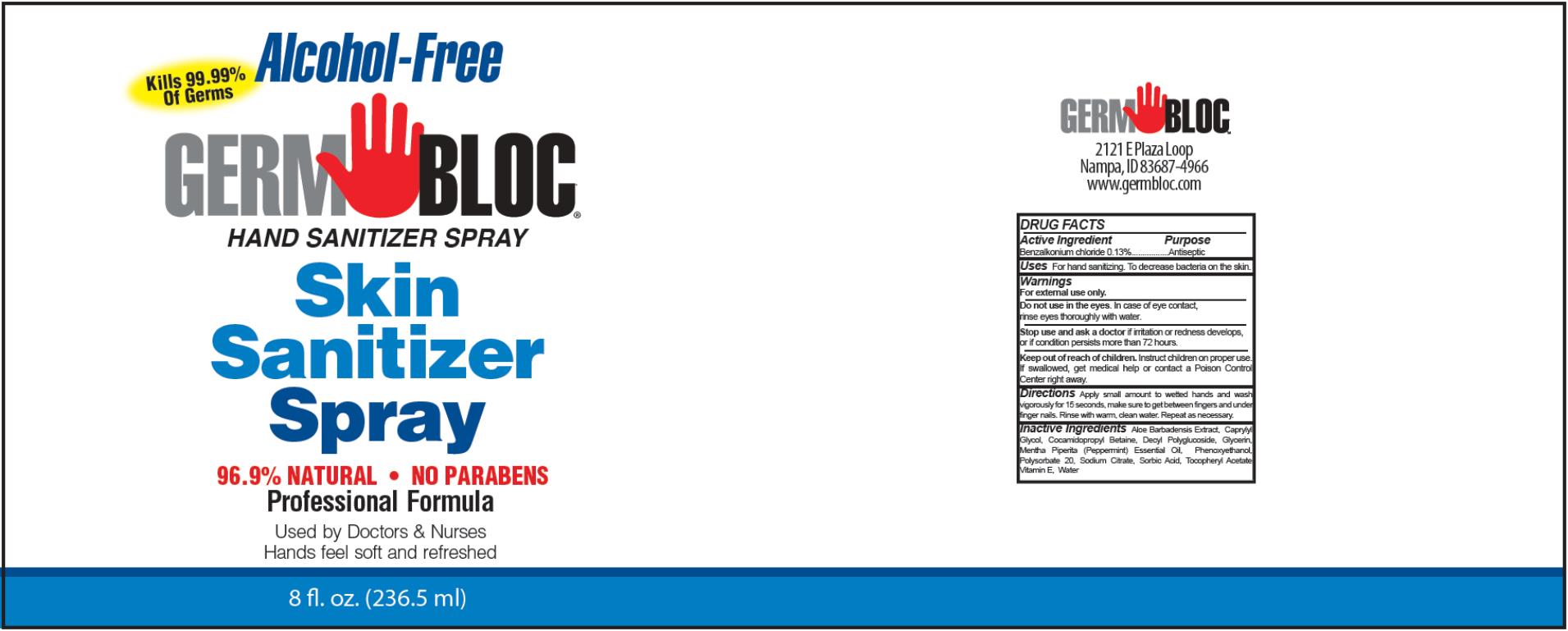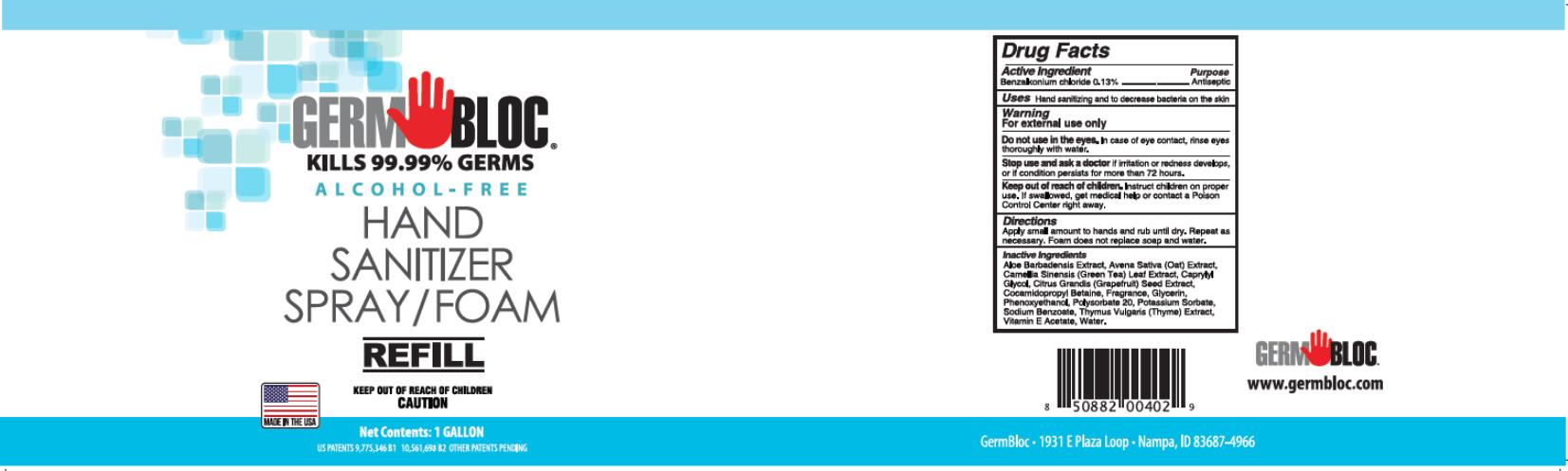 DRUG LABEL: Germ Bloc Hand Sanitizer
NDC: 69243-0810 | Form: SPRAY
Manufacturer: Willspeed Technologies LLC
Category: otc | Type: HUMAN OTC DRUG LABEL
Date: 20220114

ACTIVE INGREDIENTS: BENZALKONIUM CHLORIDE 0.0013 g/1 mL
INACTIVE INGREDIENTS: ALOE VERA LEAF; CAPRYLYL GLYCOL; COCAMIDOPROPYL BETAINE; LAURYL GLUCOSIDE; GLYCERIN; PEPPERMINT OIL; PHENOXYETHANOL; POLYSORBATE 20; SODIUM CITRATE; SORBIC ACID; ALPHA-TOCOPHEROL ACETATE; WATER

Germ Bloc Hand Sanitizer Spray

DRUG FACTS

Active Ingredient

Benzalkonium chloride 0.13%

Purpose

Antiseptic

Uses

For hand sanitizing. To decrease bacteria on the skin.

Warnings

For external use only.

Do not use in the eyes.

In case of eye contact, rinse eyes thoroughly with water.

Stop use and ask a doctor

if irritation or redness develops, or if condition persists more than 72 hours.

Keep out of reach of children.

Instruct children on proper use. If swallowed, get medical help or contact a Poison Control Center right away.

Directions

Apply small amount to wetted hands and wash vigorously for 15 seconds, make sure to get between fingers and under finger nails. Rinse with warm, clean water. Repeat as necessary.

Inactive Ingredients

Aloe Barbadensis Extract, Caprylyl Glycol, Cocamidopropyl Betaine, Decyl Polyglucoside, Glycerin, Mentha Piperita (Peppermint) Essential Oil, Phenoxyethanol, Polysorbate 20, Sodium Citrate, Sorbic Acid, Tocopheryl Acetate Vitamin E, Water

DRUG FACTS

Active Ingredient

Benzalkonium chloride 0.13%

Purpose

Antiseptic

Uses

For hand sanitizing. To decrease bacteria on the skin.

Warnings

For external use only.

Do not use in the eyes.

In case of eye contact, rinse eyes thoroughly with water.

Stop use and ask a doctor

if irritation or redness develops, or if condition persists more than 72 hours.

Keep out of reach of children.

Instruct children on proper use. If swallowed, get medical help or contact a Poison Control Center right away.

Directions

Apply small amount to wetted hands and wash vigorously for 15 seconds, make sure to get between fingers and under finger nails. Rinse with warm, clean water. Repeat as necessary.

Inactive Ingredients

Aloe Barbadensis Extract, Avena Sativa (Oat) Extract, Camellia Sinensis (Green Tea) Leaf Extract, Caprylyl Glycol, Citrus Grandis (Grapefruit) Seed Extract, Cocamidopropyl Betaine, Fragrance, Glycerin, Phenoxyethanol, Polysorbate 20, Potassium Sorbate, Sodium Benzoate, Thymus Vulgaris (Thyme) Extract, Vitamin E Acetate, Water

PRINCIPAL DISPLAY PANEL

Alcohol-Free
Kills 99.99% of Germs
GERM BLOC®
HAND SANITIZER SPRAY
Skin
Sanitizer
Spray
8 fl. oz. (236.5 ml)

PRINCIPAL DISPLAY PANEL

GERM BLOC®
KILLS 99.99% GERMS
ALCOHOL-FREE
HAND SANITIZER
SPRAY/FOAM
REFILL
Net Contents: 1 GALLON